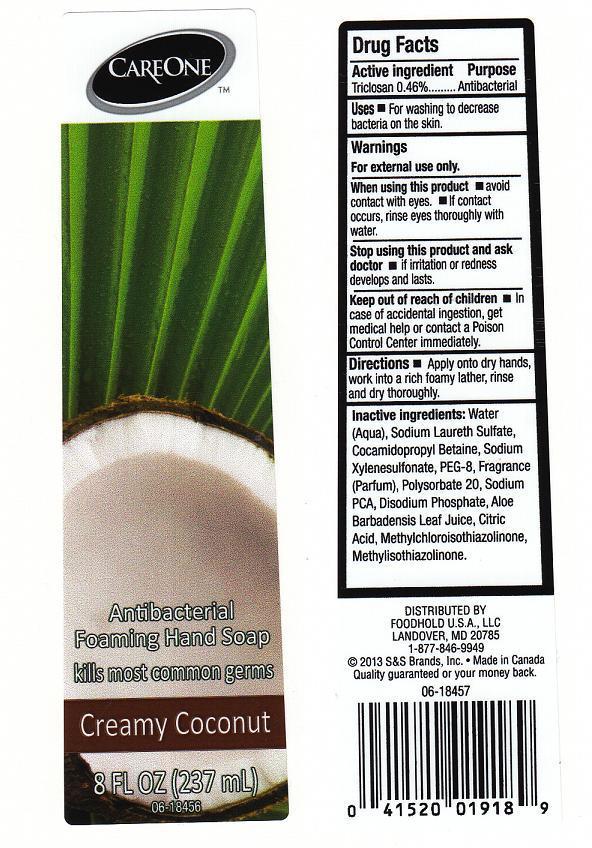 DRUG LABEL: CARE ONE
NDC: 41520-196 | Form: LIQUID
Manufacturer: AMERICAN SALES COMPANY
Category: otc | Type: HUMAN OTC DRUG LABEL
Date: 20130220

ACTIVE INGREDIENTS: TRICLOSAN 4.6 mg/1 mL
INACTIVE INGREDIENTS: WATER; SODIUM LAURETH SULFATE; COCAMIDOPROPYL BETAINE; SODIUM XYLENESULFONATE; POLYETHYLENE GLYCOL 400; POLYSORBATE 20; SODIUM PYRROLIDONE CARBOXYLATE; SODIUM PHOSPHATE, DIBASIC, ANHYDROUS; ALOE VERA LEAF; CITRIC ACID MONOHYDRATE; METHYLCHLOROISOTHIAZOLINONE; METHYLISOTHIAZOLINONE

DRUG FACTS

ACTIVE INGREDIENT

TRICLOSAN 0.46%

PURPOSE

ANTIBACTERIAL

USES

FOR WASHING TO DECREASE BACTERIA ON THE SKIN.

WARNINGS

FOR EXTERNAL USE ONLY.

WHEN USING THIS PRODUCT

AVOID CONTACT WITH EYES. IF CONTACT OCCURS, RINSE EYES THOROUGHLY WITH WATER.

STOP USING THIS PRODUCT AND ASK DOCTOR

IF IRRITATION OR REDNESS DEVELOPS AND LASTS.

KEEP OUT OF REACH OF CHILDREN

IN CASE OF ACCIDENTAL INGESTION, GET MEDICAL HELP OR CONTACT A POISON CONTROL CENTER IMMEDIATELY.

DIRECTIONS

APPLY ONTO DRY HANDS, WORK INTO A RICH FOAMY LATHER, RINSE AND DRY THOROUGHLY.

INACTIVE INGREDIENTS:

WATER (AQUA), SODIUM LAURETH SULFATE, COCAMIDOPROPYL BETAINE, SODIUM XYLENESULFONATE, PEG-8, FRAGRANCE (PARFUM), POLYSORBATE 20, SODIUM PCA, DISODIUM PHOSPHATE, ALOE BARBADENSIS LEAF JUICE, CITRIC ACID, METHYLCHLOROISOTHIAZOLINONE, METHYLISOTHIAZOLINONE.